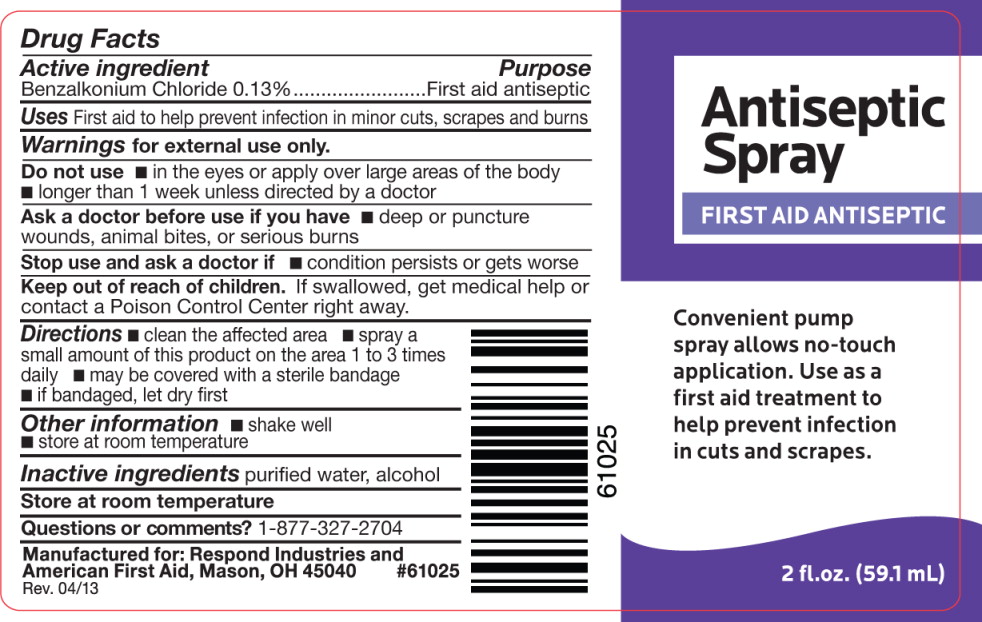 DRUG LABEL: Antiseptic
NDC: 68421-7120 | Form: LIQUID
Manufacturer: Cintas First Aid & Safety
Category: otc | Type: HUMAN OTC DRUG LABEL
Date: 20130604

ACTIVE INGREDIENTS: benzalkonium chloride 1.2478 g/1 L
INACTIVE INGREDIENTS: alcohol; water

Drug Facts

Active Ingredient

Benzalkonium Chloride 0.13%

Purpose

First Aid Antiseptic

Uses

- First aid to help prevent infection in minor cuts, scrapes and burns

Warnings

For external use only

Do not use

- in the eyes, or apply over large areas of the body
- longer than 1 week unless directed by a doctor

Ask a doctor before use if you have

- deep or puncture wounds, animal bites or serious burns

Stop use and ask a doctor if

- condition persists or gets worse

Keep out of reach of children. If swallowed, get medical help or contact a Poison Control Center right away

Directions

- clean the affected area
- spray a small amount of this product on the area 1 to 3 times daily
- may be covered with a sterile bandage
- if bandaged, let dry first

Other information

- shake well
- store at room temperature

Inactive ingredients

purified water, alcohol

STORAGE AND HANDLING

Store at room temperature

Questions or comments?

1-800-327-2704

Manufactured for: Respond Industries and American First Aid
Mason, OH 45040
#61025
Rev 04/13

PRINCIPAL DISPLAY PANEL – bottle label

Antiseptic
Spray

FIRST AID ANTISEPTIC
Convenient pump
spray allows no-touch
application. Use as a
first aid treatment to
help prevent infection
in cuts and scrapes.
2 fl. oz. (59.1 mL)